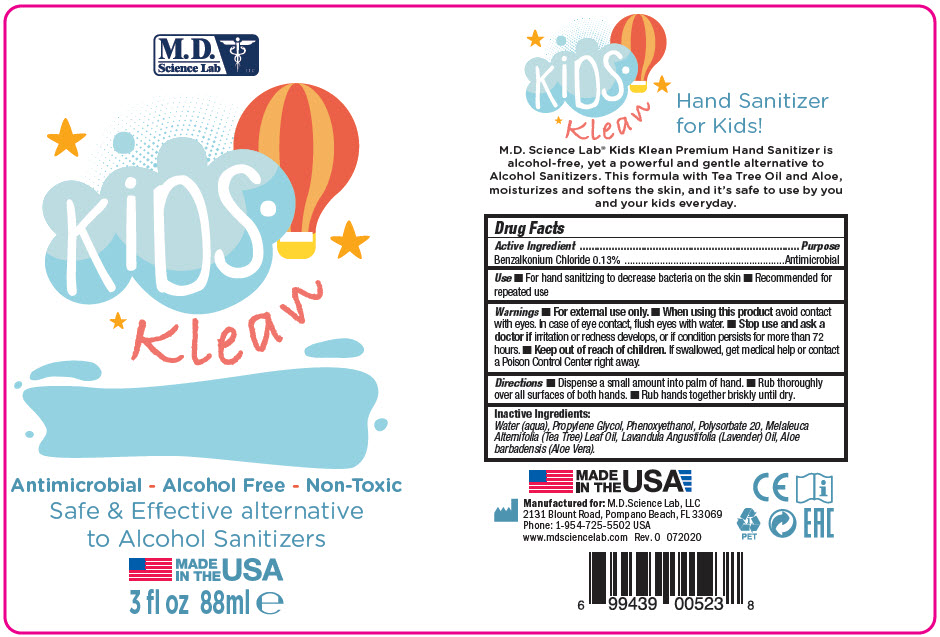 DRUG LABEL: PREMIUM HAND SANITIZER
NDC: 69898-901 | Form: LIQUID
Manufacturer: MD Science Lab LLC
Category: otc | Type: HUMAN OTC DRUG LABEL
Date: 20200807

ACTIVE INGREDIENTS: Benzalkonium Chloride 1.3 mg/1 mL
INACTIVE INGREDIENTS: Water; Propylene Glycol; Phenoxyethanol; LAVENDER OIL; TEA TREE OIL; ALOE VERA LEAF; POLYSORBATE 20

PREMIUM HAND SANITIZER

Drug Facts

Active Ingredient

Benzalkonium Chloride 0.13%

Purpose

Antimicrobial

Use

- For hand sanitizing to decrease bacteria on the skin
- Recommended for repeated use

Warnings

- For external use only.

- When using this product avoid contact with eyes. In case of eye contact, flush eyes with water.

- Stop use and ask a doctor if irritation or redness develops, or if condition persists for more than 72 hours.

- Keep out of reach of children. If swallowed, get medical help or contact a Poison Control Center right away.

Directions

- Dispense a small amount into palm of hand.
- Rub thoroughly over all surfaces of both hands.
- Rub hands together briskly until dry.

Inactive Ingredients

Water (aqua), Propylene Glycol, Phenoxyethanol, Polysorbate 20, Melaleuca Alternifolia (Tea Tree) Leaf Oil, Lavandula Angustifolia (Lavender) Oil, Aloe barbadensis (Aloe Vera).

PRINCIPAL DISPLAY PANEL - 88 ml Bottle Label

M.D.
Science Lab
LLC

KiDS
KLean

Antimicrobial - Alcohol Free - Non-Toxic
Safe & Effective alternative
to Alcohol Sanitizers

MADE
IN THE
USA

3 fl oz 88ml e